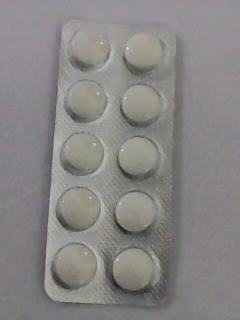 DRUG LABEL: APROFEN
NDC: 46084-021 | Form: TABLET
Manufacturer: A P J Laboratories Limited
Category: otc | Type: HUMAN OTC DRUG LABEL
Date: 20130221

ACTIVE INGREDIENTS: IBUPROFEN 200 mg/1 1
INACTIVE INGREDIENTS: CALCIUM PHOSPHATE, DIBASIC, ANHYDROUS 40 mg/1 1; STARCH, CORN 20 mg/1 1; GELATIN 2 mg/1 1; METHYLPARABEN 3 mg/1 1; TITANIUM DIOXIDE 0.1 mg/1 1; MAGNESIUM STEARATE 10 mg/1 1; TALC 10 mg/1 1; SODIUM STARCH GLYCOLATE TYPE A POTATO 20 mg/1 1; SILICON DIOXIDE 1 mg/1 1

ACTIVE INGREDIENT

Ibuprofen USP, 200 mg (NSAID)

PURPOSE

Pain reliever/fever reducer

Keep out of reach of children. In case of overdose, get medical help or contact a Poison Control Center (1-800-222-1222) right away.

INDICATIONS AND USAGE

temporarily relieves minor aches and pains due to:

headache
muscular aches
minor pain of arthritis
toothache
backache
the common cold
menstrual cramps
temporarily reduces fever

Allergy alert: Ibuprofen may cause a severe allergic reaction, especially in people allergic to aspirin. Symptoms may include:
hives
facial swelling
asthma(wheezing)
shock
skin reddening
rash
blisters
If an allergic reaction occurs, stop use and seek medical help right away.
Stomach bleeding warning: This product contains a nonsteroidal anti-inflammatory drug (NSAID), which may cause severe stomach bleeding. The chances are higher if you:
are age 60 or older
have had stomach ulcers or bleeding problems
take a blood thinning (anticoagulant) or steroid drug
take other drugs containing prescription or nonprescription NSAIDs (aspirin, ibuprofen, naproxen, or others)
have 3 or more alcoholic drinks every day while using this product
take more or for a longer time than directed

DOSAGE AND ADMINISTRATION

do not take more than directed
the smallest effective dose should be used
Adults and children 12 years and older: take 1 tablet every 4 to 6 hours while symptoms persist
if pain or fever does not respond to 1 tablet, 2 tablets may be used
do not exceed 6 tablets in 24 hours, unless directed by a doctor
Children under 12 years: ask a doctor

INACTIVE INGREDIENT

CALCIUM PHOSPHATE, DIBASIC, ANHYDROUS

INACTIVE INGREDIENT

STARCH, CORN

INACTIVE INGREDIENT

GELATIN

INACTIVE INGREDIENT

METHYLPARABEN

INACTIVE INGREDIENT

TITANIUM DIOXIDE

INACTIVE INGREDIENT

MAGNESIUM STEARATE

INACTIVE INGREDIENT

TALC

INACTIVE INGREDIENT

SODIUM STARCH GLYCOLATE TYPE A POTATO

INACTIVE INGREDIENT

SILICON DIOXIDE